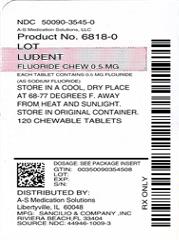 DRUG LABEL: Ludent
NDC: 50090-3545 | Form: TABLET, CHEWABLE
Manufacturer: A-S Medication Solutions
Category: other | Type: DIETARY SUPPLEMENT
Date: 20180831

ACTIVE INGREDIENTS: SODIUM FLUORIDE 0.5 mg/1 1
INACTIVE INGREDIENTS: Xylitol; Microcrystalline Cellulose; Malic Acid; Magnesium Stearate; Talc; Anhydrous Citric Acid; Sucralose

Ludent® Fluoride Chews

STATEMENT OF IDENTITY

Each 0.5 mg Fluoride Tablet Contains:

Fluoride (as Sodium Fluoride) [Each 0.5 mg Fluoride Tablet contains 0.5 mg Fluoride from 1.1 mg Sodium Fluoride (NaF).] | 0.5 mg

WARNING

KEEP THIS AND ALL MEDICATIONS OUT OF THE REACH OF CHILDREN. IF OVERDOSAGE IS SUSPECTED, SEEK PROFESSIONAL ASSISTANCE OR CONTACT A POISON CONTROL CENTER IMMEDIATELY 1-800-222-1222. TABLET SHOULD BE CHEWED. THIS PRODUCT, AS WITH ALL CHEWABLE TABLETS, IS NOT RECOMMENDED FOR CHILDREN UNDER AGE 4 DUE TO RISK OF CHOKING.

DO NOT USE IF FOIL SEAL UNDER CAP IS BROKEN OR MISSING

Directions

USE AS DIRECTED BY YOUR PHYSICIAN.

Description

White to off-white, orange flavor, round-shaped chewable tablet debossed "SCI" on one side and "1007" on the other.

See inside panel for additional information

Caution

Do not use this product if you are allergic to any of the ingredients. Take this product at least 2 hours before or after taking any products containing calcium (including milk, yogurt, other dairy products) or aluminum/magnesium hydroxide (e.g., certain antacids/laxatives). Prolonged daily ingestion of excessive fluoride may result in varying degrees of dental fluorosis. Account for all daily sources of fluoride intake.

Other Ingredients

Xylitol, microcrystalline cellulose, malic acid, magnesium stearate, talc, citric acid, natural orange flavor, sucralose.

Storage

Store in a cool, dry place at room temperature 20° - 25°C (68° - 77°F) away from heat and sunlight. Store in original container.

This medical food product is formulated to be administered orally, under the ongoing supervision of a physician and is intended for the dietary management of dental caries for which a distinctive nutritional requirement of fluoride, based on recognized scientific principles, has been established by medical evaluation.

The numeric identifier on this product's labeling is an assigned product code for use with pharmacy-level, health-insurance and state level reimbursement programs and is not intended to denote registration with the FDA.

HEALTH CLAIM

Manufactured by: Sancilio & Co., Inc.
Riviera Beach, FL 33404 USA

rev. 12/02/11